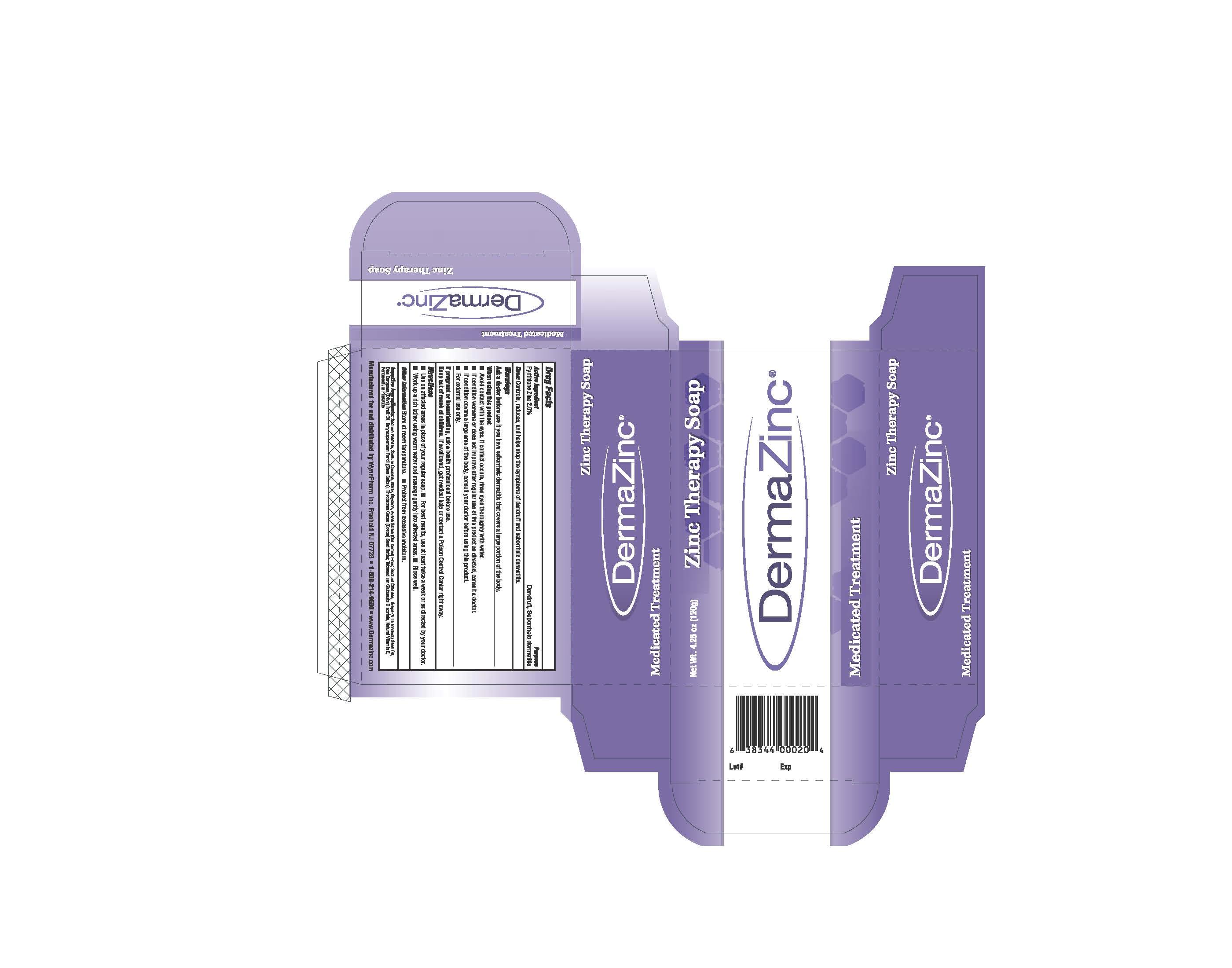 DRUG LABEL: DermaZinc
NDC: 35324-004 | Form: SOAP
Manufacturer: WynnPharm Inc
Category: otc | Type: HUMAN OTC DRUG LABEL
Date: 20251114

ACTIVE INGREDIENTS: PYRITHIONE ZINC 2 g/100 g
INACTIVE INGREDIENTS: AVENA SATIVA WHOLE; GLYCERIN; SODIUM CHLORIDE; TETRASODIUM GLUTAMATE DIACETATE; PENTASODIUM PENTETATE; SHEA BUTTER; VITAMIN E POLYETHYLENE GLYCOL SUCCINATE; OLIVE OIL; GRAPE SEED OIL; SODIUM PALMATE; SODIUM PALM KERNELATE; WATER; COCOA BUTTER

DermaZinc Soap

ACTIVE INGREDIENT

Pyrithione Zinc 2%

Keep Out of Reach of Children.

PURPOSE

Dandruff, Seborrheic Dermatitis treatment

DOSAGE AND ADMINISTRATION

-Use on affected areas in place of regular soap.

-For best results, use at least twice a week, or as directed by your doctor.

-Work up a rich lather using warm water and massage gently into affected areas.

-Rinse well.

INDICATIONS AND USAGE

Controls, reduces and helps stop the symptoms of dandruff and seborrheic dermatitis.

Warnings
■ Ask a doctor before use if you have a condition that covers a large area of the body.

When using this product avoid contact with the eyes. If contact occurs, rinse eyes thoroughly with
water.
Stop use and ask a doctor if condition worsens or does not improve after regular use of this
product as directed.

If pregnant or breast-feeding, ask a health professional before use. Keep out of reach of children.
If swallowed, get medical help or contact a Poison Control Center right away.

■ For external use only.

INACTIVE INGREDIENT

Sodium Palmate, Sodium Cocoate, Water, Glycerin, Avena Sativa (Oat Kernel) Flour, Sodium Chloride, Grape Seed Oil, Olea Europaea (Olive) Fruit Oil, Butyrospermum Parkii (Shea Butter), Theobroma Cacao (Cocoa) Seed Butter, Tetrasodium Glutamate Diacetate, Natural Vitamin E, Pentasodium Pentatate.